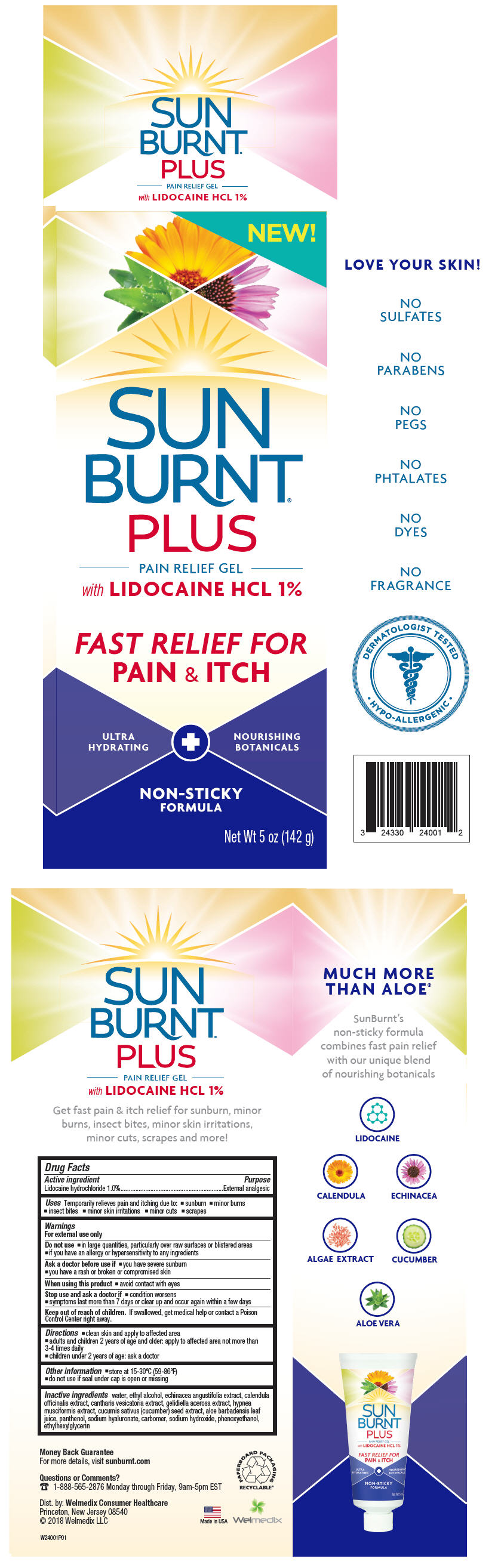 DRUG LABEL: SunBurnt PLUS Pain Relief
NDC: 24330-240 | Form: GEL
Manufacturer: Welmedix LLC dba Welmedix Consumer Healthcare
Category: otc | Type: HUMAN OTC DRUG LABEL
Date: 20180313

ACTIVE INGREDIENTS: Lidocaine Hydrochloride 1 g/100 g
INACTIVE INGREDIENTS: Water; ALCOHOL; ECHINACEA ANGUSTIFOLIA; CALENDULA OFFICINALIS FLOWERING TOP; LYTTA VESICATORIA; GELIDIELLA ACEROSA; HYPNEA MUSCIFORMIS; CUCUMBER SEED; ALOE VERA LEAF; Panthenol; HYALURONATE SODIUM; CARBOMER HOMOPOLYMER TYPE C (ALLYL PENTAERYTHRITOL CROSSLINKED); Sodium hydroxide; Phenoxyethanol; Ethylhexylglycerin

SunBurnt® PLUS Pain Relief Gel

Drug Facts

Active ingredient

Lidocaine hydrochloride 1.0%

Purpose

External analgesic

Uses

Temporarily relieves pain and itching due to:

- sunburn
- minor burns
- insect bites
- minor skin irritations
- minor cuts
- scrapes

Warnings

For external use only

Do not use

- in large quantities, particularly over raw surfaces or blistered areas
- if you have an allergy or hypersensitivity to any ingredients

Ask a doctor before use if

- you have severe sunburn
- you have a rash or broken or compromised skin

When using this product

- avoid contact with eyes

Stop use and ask a doctor if

- condition worsens
- symptoms last more than 7 days or clear up and occur again within a few days

Keep out of reach of children. If swallowed, get medical help or contact a Poison Control Center right away.

Directions

- clean skin and apply to affected area
- adults and children 2 years of age and older: apply to affected area not more than 3-4 times daily
- children under 2 years of age: ask a doctor

Other information

- store at 15-30ºC (59-86ºF)
- do not use if seal under cap is open or missing

Inactive ingredients

water, ethyl alcohol, echinacea angustifolia extract, calendula officinalis extract, cantharis vesicatoria extract, gelidiella acerosa extract, hypnea musciformis extract, cucumis sativus (cucumber) seed extract, aloe barbadensis leaf juice, panthenol, sodium hyaluronate, carbomer, sodium hydroxide, phenoxyethanol, ethylhexylglycerin

Questions or Comments?

1-888-565-2876 Monday through Friday, 9am-5pm EST

Dist. by: Welmedix Consumer Healthcare
Princeton, New Jersey 08540

PRINCIPAL DISPLAY PANEL - 142 g Tube Carton

NEW!

SUN
BURNT®
PLUS
PAIN RELIEF GEL
with LIDOCAINE HCL 1%

FAST RELIEF FOR
PAIN & ITCH

ULTRA
HYDRATING

NOURISHING
BOTANICALS

NON-STICKY
FORMULA

Net Wt 5 oz (142 g)